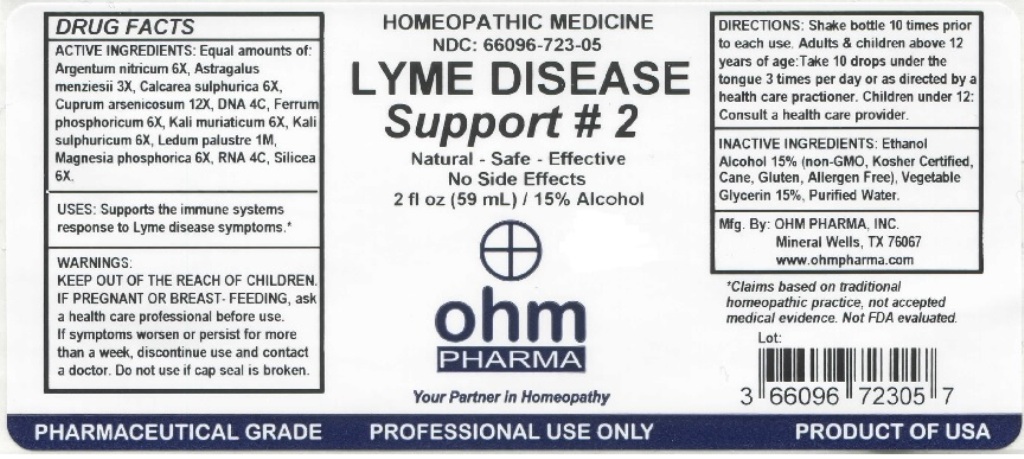 DRUG LABEL: Lyme Disease Support 2
NDC: 66096-723 | Form: LIQUID
Manufacturer: OHM PHARMA INC.
Category: homeopathic | Type: HUMAN OTC DRUG LABEL
Date: 20211229

ACTIVE INGREDIENTS: SILVER NITRATE 6 [hp_X]/59 mL; ASTRAGALUS NUTTALLII LEAF 3 [hp_X]/59 mL; CALCIUM SULFATE ANHYDROUS 6 [hp_X]/59 mL; CUPRIC ARSENITE 12 [hp_X]/59 mL; HERRING SPERM DNA 4 [hp_C]/59 mL; FERROSOFERRIC PHOSPHATE 6 [hp_X]/59 mL; POTASSIUM CHLORIDE 6 [hp_X]/59 mL; POTASSIUM SULFATE 6 [hp_X]/59 mL; RHODODENDRON TOMENTOSUM LEAFY TWIG 1 [hp_M]/59 mL; MAGNESIUM PHOSPHATE, DIBASIC TRIHYDRATE 6 [hp_X]/59 mL; SACCHAROMYCES CEREVISIAE RNA 4 [hp_C]/59 mL; SILICON DIOXIDE 6 [hp_X]/59 mL
INACTIVE INGREDIENTS: ALCOHOL; GLYCERIN; WATER

OHM Lyme Disease Support 2

ACTIVE INGREDIENT

ACTIVE INGREDIENTS: Equal amounts of: Argentum nitricum 6X, Astragalus menziesii 3X, Calcarea sulphurica 6X, Cuprum arsenicosum 12X, DNA 4C, Ferrum phosphoricum 6X, Kali muriaticum 6X, Kali sulphuricum 6X, Ledum palustre 1M, Magnesia phosphorica 6X, RNA 4C, Silicea 6X.

INDICATIONS AND USAGE

USES: Supports the immune systems response to Lyme disease symptoms.*

* Claims based on traditional homeopathic practice, not accepted medical evidence. Not FDA evaluated.

WARNINGS

WARNINGS: IF PREGNANT OR BREAST-FEEDING, ask a health care professional before use. If symptoms worsen or persist for more than a week, discontinue use and contact a doctor.

- KEEP OUT OF REACH OF CHILDREN.

DOSAGE AND ADMINISTRATION

DIRECTIONS: Shake bottle 10 times prior to each use. Adults & children above 12 years of age: Take 10 drops under the tongue 3 times per day or as directed by a health care practioner. Children under 12: Consult a health care provider.

Do not use if cap seal is broken.

INACTIVE INGREDIENT

INACTIVE INGREDIENTS: Ethanol Alcohol 15% (non-GMO, Kosher Certified, Cane, Gluten, Allergen Free), Vegetable Glycerin 15%, Purified Water.

QUESTIONS

Mfg. By: OHM PHARMA, INC. Mineral Wells, TX 76067

www.ohmpharma.com

PACKAGE LABEL

HOMEOPATHIC MEDICINE

NDC: 66096-723-05

LYME DISEASE Support #2

Natural - Safe - Effective

No Side Effects

2 fl oz (59mL) / 15% Alcohol

PRODUCT OF USA

PURPOSE

Supports the immune systems response to Lyme disease symptoms.